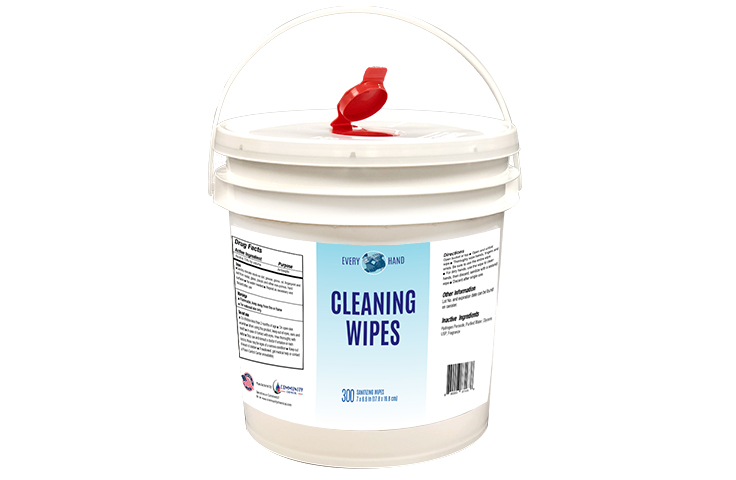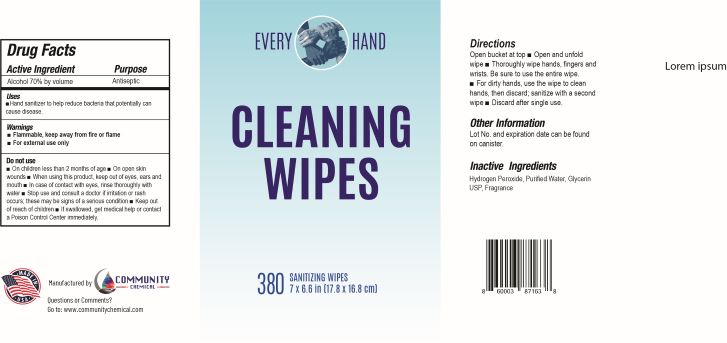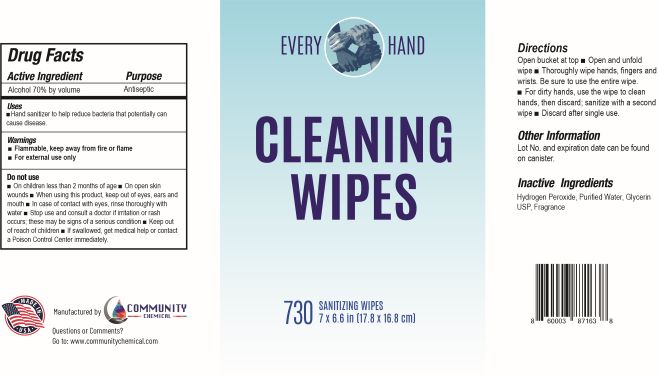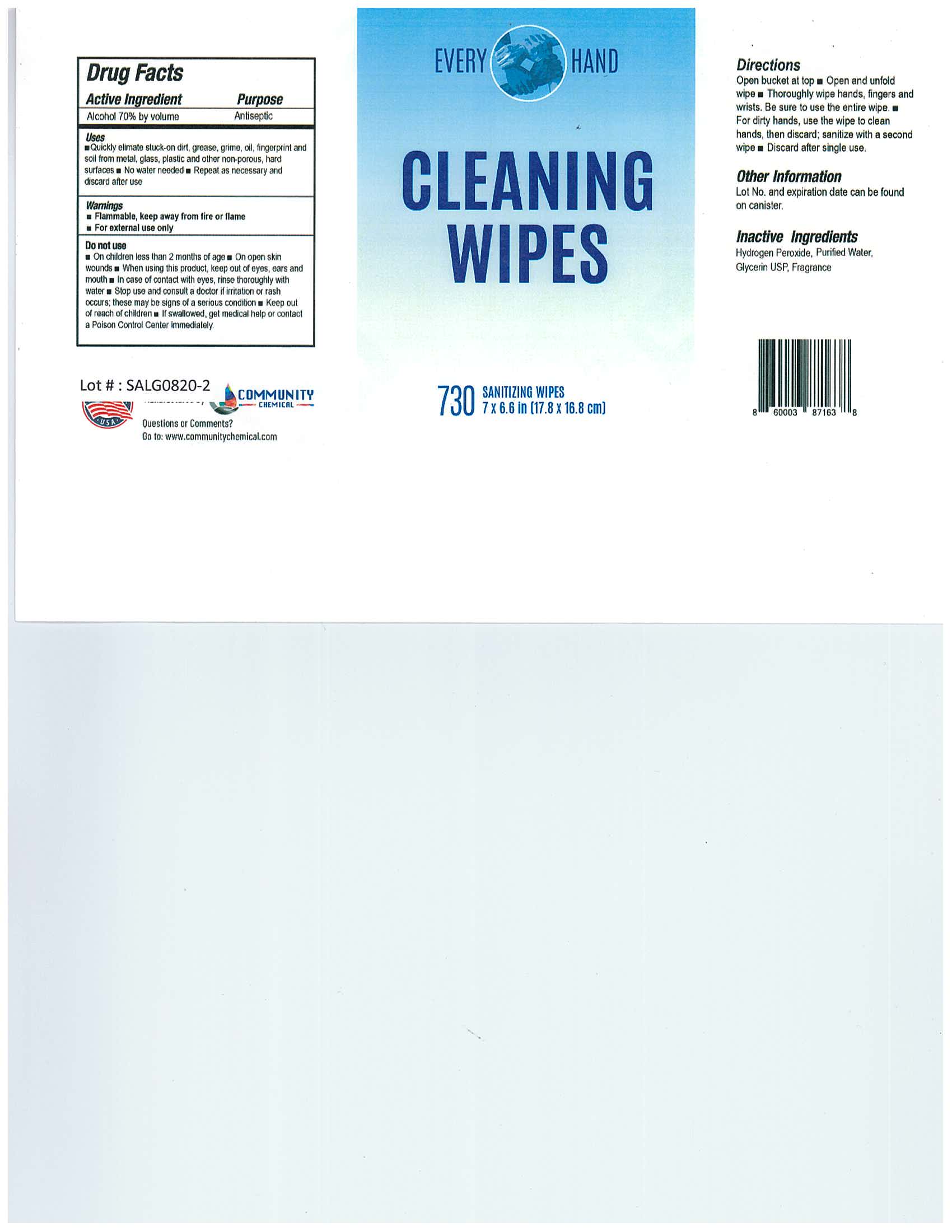 DRUG LABEL: Hand Sanitizer Wipes
NDC: 77386-904 | Form: LIQUID
Manufacturer: Community Chemical
Category: otc | Type: HUMAN OTC DRUG LABEL
Date: 20220114

ACTIVE INGREDIENTS: ALCOHOL 80 mL/80 mL
INACTIVE INGREDIENTS: WATER 1 mL/80 mL; GLYCERIN 1.45 mL/80 mL; HYDROGEN PEROXIDE 0.125 mL/80 mL

Hand Sanitizer Wipes

Alcohol 70% v/v. Purpose: Antiseptic

77386-904-91 Hand Sanitizer Wipes

Hand Sanitizer Wipes

1100 g NDC: 77386-903-91

ACTIVE INGREDIENT

77386-904-91 Hand Sanitizer Wipes

INACTIVE INGREDIENT

glycerin, hydrogen peroxide, purified water USP

DOSAGE AND ADMINISTRATION

Place enough product on to cover all surfaces. Rub hands together until dry.

Supervise children under 6 years of age when using this product to avoid swallowing.

Hand Cleaning Wipes

730 ct Cleaning Wipes

380 ct Cleaning Wipes

300 ct Cleaning Wipes